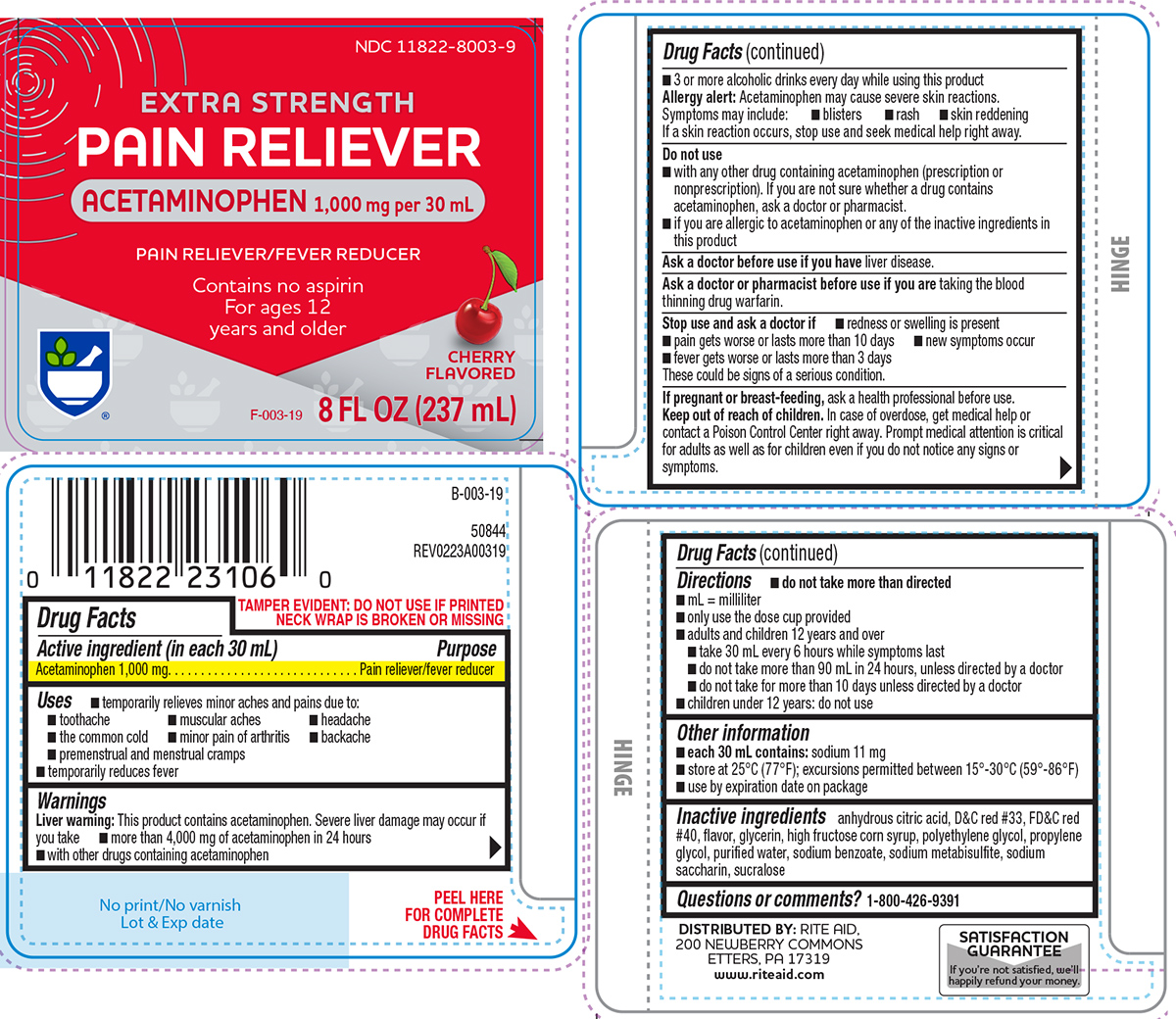 DRUG LABEL: Pain Reliever
NDC: 11822-8003 | Form: SOLUTION
Manufacturer: Rite Aid Corporation
Category: otc | Type: HUMAN OTC DRUG LABEL
Date: 20260202

ACTIVE INGREDIENTS: ACETAMINOPHEN 1000 mg/30 mL
INACTIVE INGREDIENTS: ANHYDROUS CITRIC ACID; D&C RED NO. 33; FD&C RED NO. 40; GLYCERIN; HIGH FRUCTOSE CORN SYRUP; POLYETHYLENE GLYCOL, UNSPECIFIED; PROPYLENE GLYCOL; WATER; SODIUM BENZOATE; SODIUM METABISULFITE; SACCHARIN SODIUM; SUCRALOSE

Rite Aid 44-003

Active ingredient (in each 30 mL)

Acetaminophen 1,000 mg

Purpose

Pain reliever/fever reducer

Uses

- temporarily relieves minor aches and pains due to:
  - toothache
  - muscular aches
  - headache
  - the common cold
  - minor pain of arthritis
  - backache
  - premenstrual and menstrual cramps
- temporarily reduces fever

Warnings

Liver warning: This product contains acetaminophen. Severe liver damage may occur if you take

- more than 4,000 mg of acetaminophen in 24 hours
- with other drugs containing acetaminophen
- 3 or more alcoholic drinks every day while using this product

Allergy alert: Acetaminophen may cause severe skin reactions. Symptoms may include:

- blisters
- rash
- skin reddening

If a skin reaction occurs, stop use and seek medical help right away.

Do not use

- with any other drug containing acetaminophen (prescription or nonprescription). If you are not sure whether a drug contains acetaminophen, ask a doctor or pharmacist.
- if you are allergic to acetaminophen or any of the inactive ingredients in this product

Ask a doctor before use if you have

liver disease.

Ask a doctor or pharmacist before use if you are

taking the blood thinning drug warfarin.

Stop use and ask a doctor if

- redness or swelling is present
- pain gets worse or lasts more than 10 days
- new symptoms occur
- fever gets worse or lasts more than 3 days

These could be signs of a serious condition.

If pregnant or breast-feeding,

ask a health professional before use.

Keep out of reach of children.

In case of overdose, get medical help or contact a Poison Control Center right away. Prompt medical attention is critical for adults as well as for children even if you do not notice any signs or symptoms.

Directions

- do not take more than directed
- mL = milliliter
- only use the dose cup provided
- adults and children 12 years and over
  - take 30 mL every 6 hours while symptoms last
  - do not take more than 90 mL in 24 hours, unless directed by a doctor
  - do not take for more than 10 days unless directed by a doctor
- children under 12 years: do not use

Other information

- each 30 mL contains: sodium 11 mg
- store at 25°C (77°F); excursions permitted between 15°-30°C (59°-86°F)
- use by expiration date on package

Inactive ingredients

anhydrous citric acid, D&C red #33, FD&C red #40, flavor, glycerin, high fructose corn syrup, polyethylene glycol, propylene glycol, purified water, sodium benzoate, sodium metabisulfite, sodium saccharin, sucralose

Questions or comments?

1-800-426-9391

Principal display panel

NDC 11822-8003-9

EXTRA STRENGTH
PAIN RELIEVER
ACETAMINOPHEN 1,000 mg per 30 mL

PAIN RELIEVER/FEVER REDUCER
Contains no aspirin
For ages 12
years and older

CHERRY
FLAVORED

8 FL OZ (237 mL)

TAMPER EVIDENT: DO NOT USE IF PRINTED
NECK WRAP IS BROKEN OR MISSING

50844
REV0223A00319

DISTRIBUTED BY: RITE AID,
200 NEWBERRY COMMONS
ETTERS, PA 17319
www.riteaid.com

SATISFACTION
GUARANTEE
If you’re not satisfied, we’ll
happily refund your money.

Rite Aid 44-003